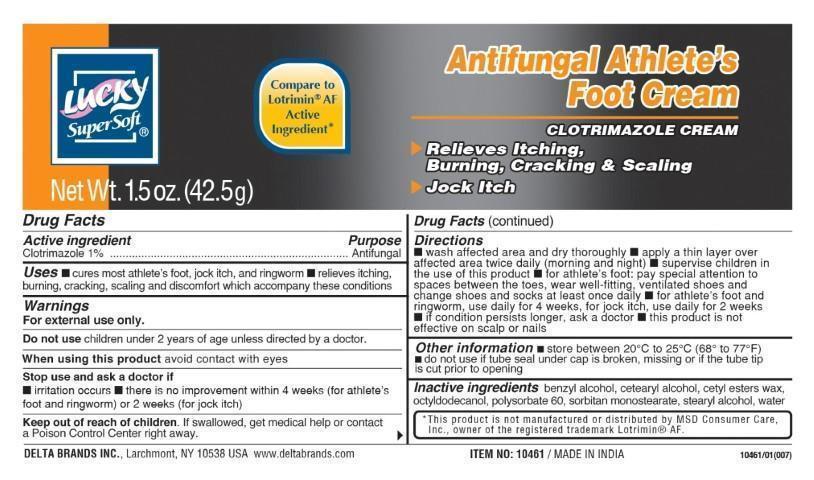 DRUG LABEL: Lucky SuperSoft
NDC: 47046-173 | Form: CREAM
Manufacturer: Anicare Pharmaceuticals Pvt. Ltd.
Category: otc | Type: HUMAN OTC DRUG LABEL
Date: 20201220

ACTIVE INGREDIENTS: CLOTRIMAZOLE 1 g/100 g
INACTIVE INGREDIENTS: BENZYL ALCOHOL; CETOSTEARYL ALCOHOL; CETYL ESTERS WAX; OCTYLDODECANOL; POLYSORBATE 60; SORBITAN MONOSTEARATE; STEARYL ALCOHOL; WATER

Antifungal Athletes Foot Cream

Active Ingredient

Clotrimazole 1%

Purpose

Antifungal

Uses

■ cures most athlete's foot, jock itch, and ringworm ■ relieves itching, burning, cracking, scaling and discomfort which accompany these conditions

Warnings

For external use only.

Do not use

children under 2 years of age unless directed by a doctor

When using this product

avoid contact with eyes

Stop use and ask a doctor if

■ irritation occurs ■ there is no improvement within 4 weeks (for athlete's foot and ringworm) or 2 weeks (jock itch)

Keep out of reach of children

If swallowed, get medical help or contact a Poison Control Center immediately

Directions

■ wash affected area and dry thoroughly ■ apply a thin layer over affected area twice daily (morning and night) ■ supervise children in the use of this product ■ for athlete's foot, pay special attention to spaces between the toes, wear well-fitting, ventilated shoes and change shoes and socks at least once a day ■ for athlete's foot and ringworm use daily for 4 weeks, for jock itch use daily for 2 weeks ■ if conditions persist longer, ask a doctor ■ this product is not effective on the scalp or nails.

Other Information

■ store between 20 to 25C (68 to 77F) ■ do not use if tube seal under cap is broken, missing or if the tube tip is cut prior to opening

Inactive Ingredients

benzyl alcohol, cetearyl alcohol, cetyl esters wax, octyldodecanol, polysorbate 60, sorbitan monostearate, stearyl alcohol, water